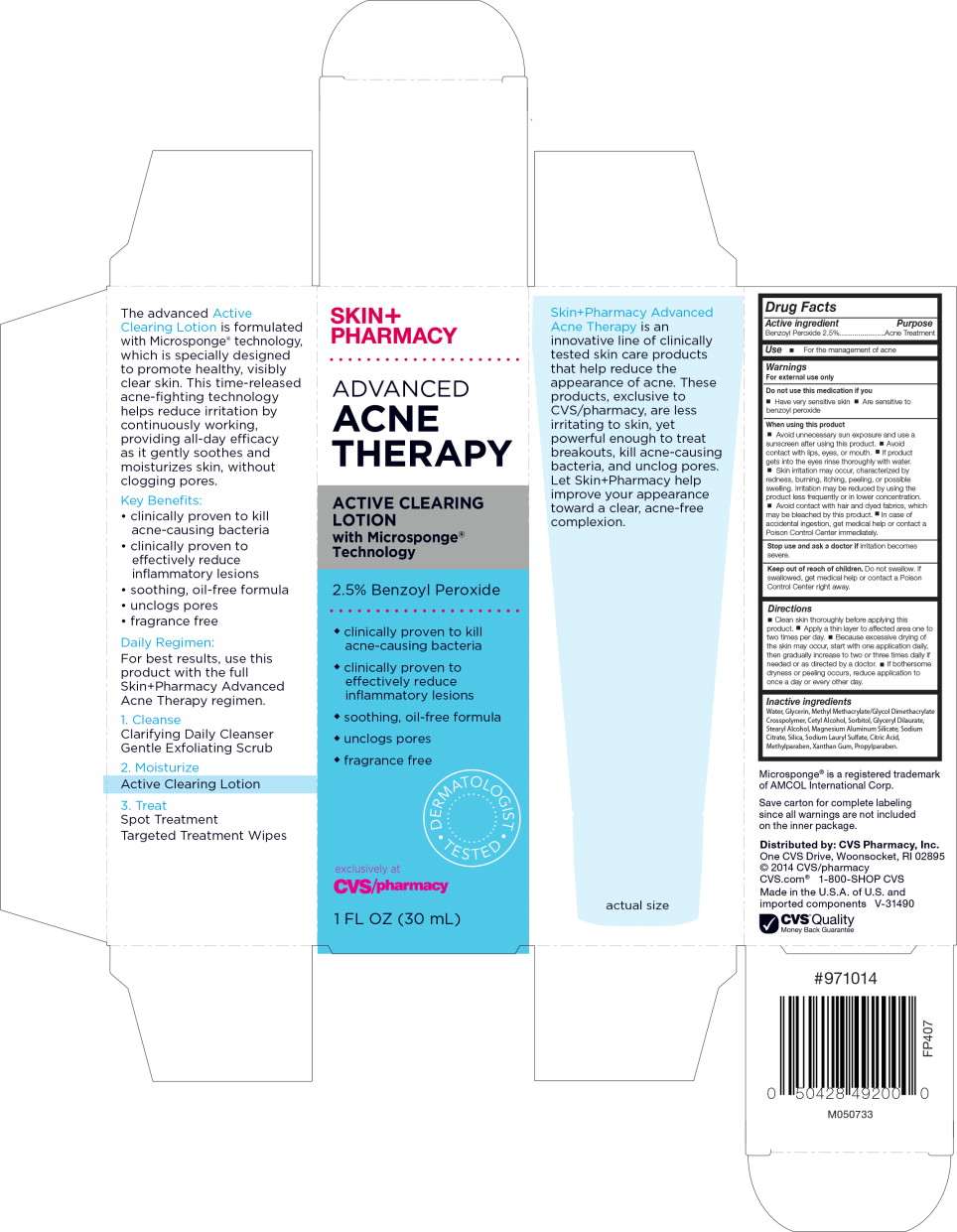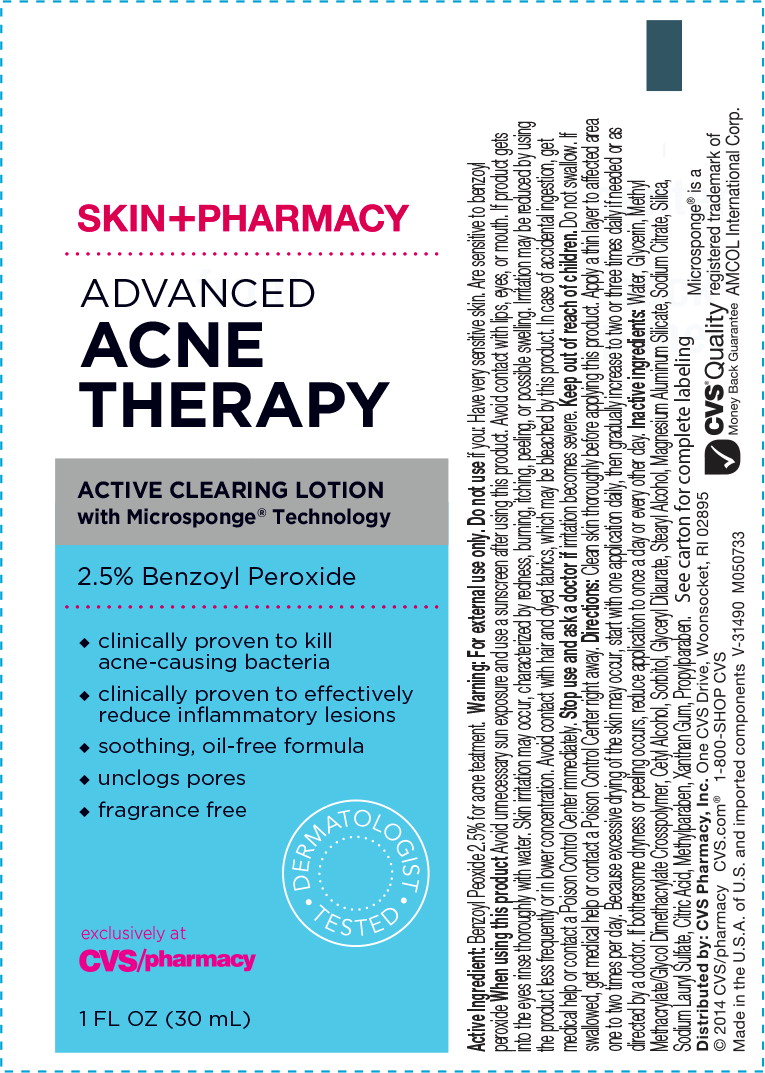 DRUG LABEL: SkinPharmacy Advanced Acne Therapy Active Clearing
NDC: 69842-076 | Form: LIQUID
Manufacturer: CVS Health
Category: otc | Type: HUMAN OTC DRUG LABEL
Date: 20170314

ACTIVE INGREDIENTS: benzoyl peroxide 25 mg/1 mL
INACTIVE INGREDIENTS: water; glycerin; methyl methacrylate/glycol dimethacrylate crosspolymer; cetyl alcohol; sorbitol; glyceryl dilaurate; stearyl alcohol; magnesium aluminum silicate; sodium citrate; silicon dioxide; sodium lauryl sulfate; citric acid monohydrate; methylparaben; xanthan gum; propylparaben

Drug Facts

Active Ingredient

Benzoyl Peroxide 2.5%

Purpose

Acne Treatment

Use

- For the management of acne

Warnings

For external use only

Do not use this medication if you

- Have very sensitive skin
- Are sensitive to benzoyl peroxide

When using this product

- Avoid unnecessary sun exposure and use a sunscreen after using this product.
- Avoid contact with lips, eyes, or mouth.
- If product gets into the eyes rinse thoroughly with water.
- Skin irritation may occur, characterized by redness, burning, itching, peeling, or possible swelling. Irritation may be reduced by using the product less frequently or in lower concentration.
- Avoid contact with hair and dyed fabrics, which may be bleached by this product.
- In case of accidental ingestion, get medical help or contact a Poison Control Center immediately.

Stop use and ask a doctor if irritation becomes severe.

Keep out of reach of children. Do not swallow. If swallowed, get medical help or contact a Poison Control Center right away.

Directions

- Clean skin thoroughly before applying this product.
- Apply a thin layer to affected area one to two times per day.
- Because excessive drying of the skin may occur, start with one application daily, then gradually increase to two or three times daily if needed or as directed by a doctor.
- If bothersome dryness or peeling occurs, reduce application to once a day or every other day.

Inactive ingredients

Water, Glycerin, Methyl Methacrylate/Glycol Dimethacrylate Crosspolymer, Cetyl Alcohol, Sorbitol, Glyceryl Dilaurate, Stearyl Alcohol, Magnesium Aluminum Silicate, Sodium Citrate, Silica, Sodium Lauryl Sulfate, Citric Acid, Methylparaben, Xanthan Gum, Propylparaben.

Microsponge® is a registered trademark of AMCOL International Corp.

Save carton for complete labeling since all warnings are not included on the inner package.

Distributed by: CVS Pharmacy, Inc.

One CVS Drive, Woonsocket, RI 02895

© 2014 CVS/pharmacy

CVS.com® 1-800-SHOP CVS

Made in the U.S.A. of U.S. and imported components V-31490

CVS® Quality

Money Back Guarantee

#971014

M050733

FP407

Principal Display Panel - Carton Label

SKIN+
PHARMACY

ADVANCED
ACNE
THERAPY

ACTIVE CLEARING LOTION
with Microsponge® Technology

2.5% Benzoyl Peroxide

- clinically proven to kill acne-causing bacteria
- clinically proven to effectively reduce inflammatory lesions
- soothing, oil-free formula
- unclogs pores
- fragrance free

DERMATOLOGIST TESTED

exclusively at
CVS/pharmacy

1 FL OZ (30 mL)

Principal Display Panel - Tube Label

SKIN+PHARMACY

ADVANCED
ACNE
THERAPY

ACTIVE CLEARING LOTION
with Microsponge® Technology

2.5% Benzoyl Peroxide

- clinically proven to kill acne-causing bacteria
- clinically proven to effectively reduce inflammatory lesions
- soothing, oil-free formula
- unclogs pores
- fragrance free

DERMATOLOGIST TESTED

exclusively at
CVS/pharmacy

1 FL OZ (30 mL)